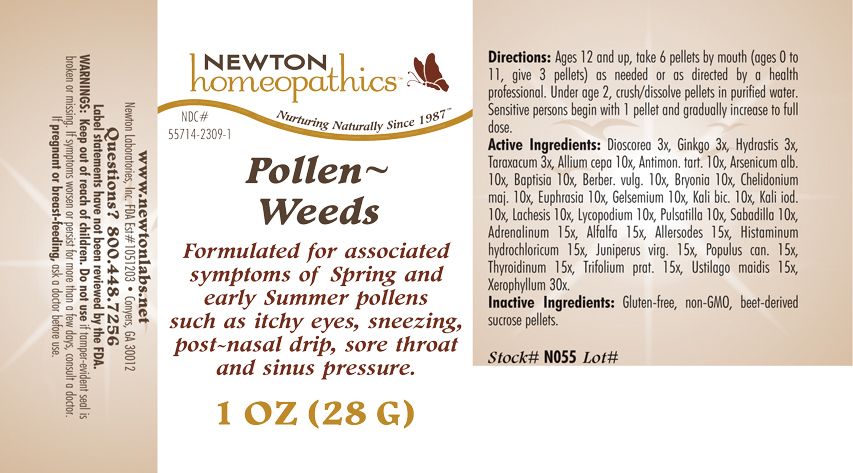 DRUG LABEL: Pollen Weeds 
NDC: 55714-2309 | Form: PELLET
Manufacturer: Newton Laboratories, Inc.
Category: homeopathic | Type: HUMAN OTC DRUG LABEL
Date: 20110301

ACTIVE INGREDIENTS: Xerophyllum Asphodeloides 30 [hp_X]/1 g; Epinephrine 15 [hp_X]/1 g; Alfalfa 15 [hp_X]/1 g; Aletris Farinosa Root 15 [hp_X]/1 g; Artemisia Vulgaris Root 15 [hp_X]/1 g; Bellis Perennis 15 [hp_X]/1 g; Dysphania Ambrosioides 15 [hp_X]/1 g; Lycopus Virginicus 15 [hp_X]/1 g; Phytolacca Americana Root 15 [hp_X]/1 g; Populus Tremuloides Leaf 15 [hp_X]/1 g; Populus Tremuloides Bark 15 [hp_X]/1 g; Ptelea Trifoliata Bark 15 [hp_X]/1 g; Sambucus Nigra Flowering Top 15 [hp_X]/1 g; Trillium Erectum Root 15 [hp_X]/1 g; Elymus Repens Root 15 [hp_X]/1 g; Urtica Urens 15 [hp_X]/1 g; Wyethia Helenioides Root 15 [hp_X]/1 g; Yucca Filamentosa 15 [hp_X]/1 g; Avena Sativa Pollen 15 [hp_X]/1 g; Cynosurus Cristatus Pollen 15 [hp_X]/1 g; Echinochloa Crus-galli Pollen 15 [hp_X]/1 g; Poa Pratensis Pollen 15 [hp_X]/1 g; Agrostis Gigantea Pollen 15 [hp_X]/1 g; Bromus Secalinus Pollen 15 [hp_X]/1 g; Alopecurus Pratensis Pollen 15 [hp_X]/1 g; Phleum Pratense Pollen 15 [hp_X]/1 g; Festuca Pratensis Pollen 15 [hp_X]/1 g; Holcus Lanatus Pollen 15 [hp_X]/1 g; Lolium Perenne Pollen 15 [hp_X]/1 g; Fagus Sylvatica Pollen 15 [hp_X]/1 g; Betula Pendula Pollen 15 [hp_X]/1 g; Quercus Alba Pollen 15 [hp_X]/1 g; Fraxinus Excelsior Pollen 15 [hp_X]/1 g; Corylus Americana Pollen 15 [hp_X]/1 g; Populus Nigra Pollen 15 [hp_X]/1 g; Platanus Orientalis Pollen 15 [hp_X]/1 g; Ulmus Glabra Pollen 15 [hp_X]/1 g; Salix Alba Pollen 15 [hp_X]/1 g; Narcissus Pseudonarcissus 15 [hp_X]/1 g; Rosa Canina Flower 15 [hp_X]/1 g; Lilium Candidum Flower 15 [hp_X]/1 g; Primula Vulgaris 15 [hp_X]/1 g; Dianthus Caryophyllus Flower 15 [hp_X]/1 g; Ulex Europaeus Flower 15 [hp_X]/1 g; Cytisus Scoparius Pollen 15 [hp_X]/1 g; Calluna Vulgaris Pollen 15 [hp_X]/1 g; Crataegus Monogyna Pollen 15 [hp_X]/1 g; Histamine Dihydrochloride 15 [hp_X]/1 g; Juniperus Virginiana Twig 15 [hp_X]/1 g; Populus Balsamifera Leaf Bud 15 [hp_X]/1 g; Thyroid, Unspecified 15 [hp_X]/1 g; Trifolium Pratense Flower 15 [hp_X]/1 g; Ustilago Maydis 15 [hp_X]/1 g; Onion 10 [hp_X]/1 g; Antimony Potassium Tartrate 10 [hp_X]/1 g; Arsenic Trioxide 10 [hp_X]/1 g; Baptisia Tinctoria Root 10 [hp_X]/1 g; Berberis Vulgaris Root Bark 10 [hp_X]/1 g; Bryonia Alba Root 10 [hp_X]/1 g; Chelidonium Majus 10 [hp_X]/1 g; Euphrasia Stricta 10 [hp_X]/1 g; Gelsemium Sempervirens Root 10 [hp_X]/1 g; Potassium Dichromate 10 [hp_X]/1 g; Potassium Iodide 10 [hp_X]/1 g; Lachesis Muta Venom 10 [hp_X]/1 g; Lycopodium Clavatum Spore 10 [hp_X]/1 g; Pulsatilla Vulgaris 10 [hp_X]/1 g; Schoenocaulon Officinale Seed 10 [hp_X]/1 g; Dioscorea Villosa Tuber 3 [hp_X]/1 g; Ginkgo 3 [hp_X]/1 g; Goldenseal 3 [hp_X]/1 g; Taraxacum Officinale 3 [hp_X]/1 g; Anthoxanthum Odoratum Pollen 15 [hp_X]/1 g
INACTIVE INGREDIENTS: Water; Alcohol

Pollen - Weeds

INDICATIONS & USAGE SECTION

Formulated for associated symptoms of Spring and early Summer pollens such as itchy eyes, sneezing, post-nasal drip, sore throat and sinus pressure.

DOSAGE & ADMINISTRATION SECTION

Directions: Ages 12 and up, take 6 pellets by mouth (ages 0 to 11, give 3 pellets) as needed or as directed by a health professional. Under 2, crush/dissolve pellets in purified water. Sensitive persons begin with 1 pellet and gradually increase to full dose.

OTC - ACTIVE INGREDIENT SECTION

Xerophyllum asphodeloides 30, Adrenalinum 15x, Alfalfa 15x, Allersodes 15x, Histaminum hydrochloricum 15x, Juniperus virg. 15x, Populus can. 15x, Thyroidinum 15x, Trifolium prat. 15x, Ustilago maidis 15x, Allium cepa 10x, Antimon. tart. 10x, Arsenicum alb. 10x, Baptisia 10x, Berber. vulg. 10x, Bryonia 10x, Chelidonium majus 10x, Euphrasia 10x, Gelsemium 10x, Kali bic. 10x, Kali iod. 10x, Lachesis 10x, Lycopodium 10x, Pulsatilla 10x, Sabadilla 10x, Dioscorea 3x, Ginkgo 3x, Hydrastis 3x, Taraxacum 3x.

OTC - PURPOSE SECTION

Formulated for associated symptoms of Spring and early Summer pollens such as itchy eyes, sneezing, post-nasal drip, sore throat and sinus pressure.

INACTIVE INGREDIENT SECTION

Inactive Ingredients: Gluten-free, non-GMO, beet-derived sucrose pellets.

QUESTIONS SECTION

www.newtonlabs.net Newton Laboratories, Inc. FDA Est # 1051203 - Conyers, GA 30012
Questions? 1.800.448.7256

WARNINGS SECTION

Warnings: Keep out of reach of children. Do no use if tamper-evident seal is broken or missing. If symptoms worsen or persist for more than a few days, consult a doctor. If pregnant or breast-feeding, ask a doctor before use.

OTC - PREGNANCY OR BREAST FEEDING SECTION

If pregnant or breast-feeding, ask a doctor before use.

OTC - KEEP OUT OF REACH OF CHILDREN SECTION

Keep out of reach of children.